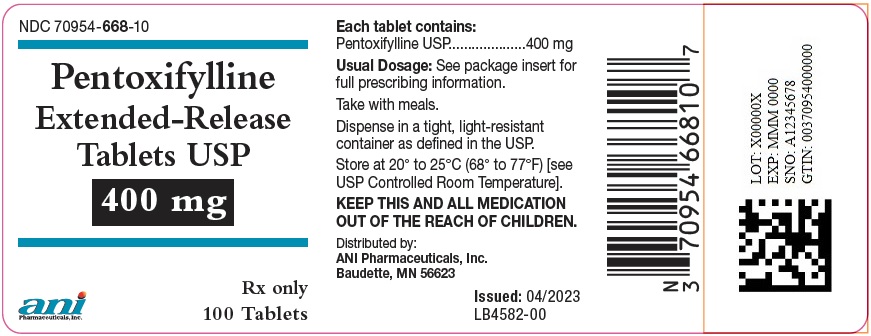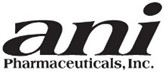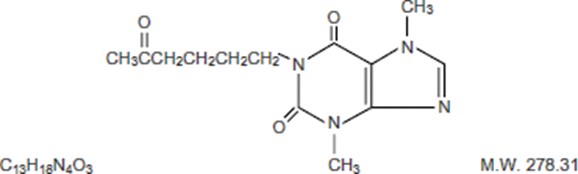 DRUG LABEL: Pentoxifylline
NDC: 70954-668 | Form: TABLET, EXTENDED RELEASE
Manufacturer: ANI Pharmaceuticals, Inc.
Category: prescription | Type: HUMAN PRESCRIPTION DRUG LABEL
Date: 20251107

ACTIVE INGREDIENTS: PENTOXIFYLLINE 400 mg/1 1
INACTIVE INGREDIENTS: HYPROMELLOSE 2910 (10000 MPA.S); POVIDONE K30; TALC; MAGNESIUM STEARATE; HYPROMELLOSE, UNSPECIFIED; TITANIUM DIOXIDE; D&C YELLOW NO. 10 ALUMINUM LAKE; FD&C YELLOW NO. 6; MALTODEXTRIN; POLYETHYLENE GLYCOL, UNSPECIFIED

Pentoxifylline Extended-Release Tablets USP
Rx only

DESCRIPTION

Pentoxifylline Extended-Release Tablets USP for oral administration contain 400 mg of the active drug and the following inactive ingredients: hypromellose, povidone, talc, magnesium stearate, maltodextrin, polyethylene glycol, titanium dioxide, triacetin, D&C yellow #10 aluminum lake and FD&C yellow #6 in an extended-release formulation. Pentoxifylline is a tri-substituted xanthine derivative designated chemically as 3,7-Dihydro-3,7-dimethyl-1-(5-oxohexyl)-1H‑purine-2,6-dione that, unlike theophylline, is a hemorrheologic agent, i.e. an agent that affects blood viscosity. Pentoxifylline is soluble in water and ethanol, and sparingly soluble in toluene.

The chemical structure is:

Pentoxifylline Extended-Release Tablets USP comply with USP dissolution test 7.

CLINICAL PHARMACOLOGY

Mode of Action

Pentoxifylline and its metabolites improve the flow properties of blood by decreasing its viscosity. In patients with chronic peripheral arterial disease, this increases blood flow to the affected microcirculation and enhances tissue oxygenation. The precise mode of action of pentoxifylline and the sequence of events leading to clinical improvement are still to be defined. Pentoxifylline administration has been shown to produce dose-related hemorrheologic effects, lowering blood viscosity, and improving erythrocyte flexibility. Leukocyte properties of hemorrheologic importance have been modified in animal and in vitro human studies. Pentoxifylline has been shown to increase leukocyte deformability and to inhibit neutrophil adhesion and activation. Tissue oxygen levels have been shown to be significantly increased by therapeutic doses of pentoxifylline in patients with peripheral arterial disease.

Pharmacokinetics and Metabolism

After oral administration in aqueous solution pentoxifylline is almost completely absorbed. It undergoes a first-pass effect and the various metabolites appear in plasma very soon after dosing. Peak plasma levels of the parent compound and its metabolites are reached within 1 hour. The major metabolites are Metabolite I (1-[5-hydroxyhexyl]-3,7-dimethylxanthine) and Metabolite V (1-[3-carboxypropyl]-3,7-dimethylxanthine), and plasma levels of these metabolites are 5 and 8 times greater, respectively, than pentoxifylline.

Following oral administration of aqueous solutions containing 100 to 400 mg of pentoxifylline, the pharmacokinetics of the parent compound and Metabolite I are dose-related and not proportional (non-linear), with half-life and area under the blood-level time curve (AUC) increasing with dose. The elimination kinetics of Metabolite V are not dose-dependent. The apparent plasma half-life of pentoxifylline varies from 0.4 to 0.8 hours and the apparent plasma half-lives of its metabolites vary from 1 to 1.6 hours. There is no evidence of accumulation or enzyme induction (Cytochrome P450) following multiple oral doses.

Excretion is almost totally urinary; the main biotransformation product is Metabolite V. Essentially no parent drug is found in the urine. Despite large variations in plasma levels of parent compound and its metabolites, the urinary recovery of Metabolite V is consistent and shows dose proportionality. Less than 4% of the administered dose is recovered in feces. Food intake shortly before dosing delays absorption of an immediate-release dosage form but does not affect total absorption. The pentoxifylline AUC was increased and elimination rate decreased in an older population (60-68 years, n=6) compared to younger individuals (22-30 years, n=6) (see PRECAUTIONS, Geriatric Use).

After administration of the 400 mg Pentoxifylline Extended-Release Tablet, plasma levels of the parent compound and its metabolites reach their maximum within 2 to 4 hours and remain constant over an extended period of time. Coadministration of Pentoxifylline Extended-Release Tablets with meals resulted in an increase in mean AUC and Cmax of about 1.1 and 1.3 fold for pentoxifylline, respectively. Cmax for Metabolite I also increased about1.2 fold. The extended release of pentoxifylline from the tablet eliminates peaks and troughs in plasma levels for improved gastrointestinal tolerance.

Patients with Hepatic Impairment

In patients with mild to moderate liver impairment AUC and Cmax of pentoxifylline increased 6.5 and 7.5 fold, respectively, after a single 400 mg dose of Pentoxifylline Extended-Release Tablets. AUC and Cmax of the active Metabolite I also increased 6.9 and 8.2 fold, respectively, in hepatic impaired subjects.

Pentoxifylline Extended-Release Tablets have not been studied in patients with severe hepatic failure.

Patients with Renal Impairment

In patients with mild, moderate, or severe renal impairment the exposure to pentoxifylline and its active Metabolite I are not increased. In contrast, AUC0-tss and Cmax of the active Metabolite V in patients with mild to moderate renal impairment increased 2.4 and 2.1 fold, respectively, with a 400 mg TID regimen of Pentoxifylline Extended-Release Tablets. In severe renal impairment AUC0-tss and Cmax of the active Metabolite V increased 12.9 and 10.6 fold, respectively, with a 400 mg Pentoxifylline Extended-Release Tablet TID regimen. The increase in exposure to Metabolite V is only slightly smaller in both renal impairment groups if Pentoxifylline Extended-Release Tablets are administered BID.

INDICATIONS AND USAGE

Pentoxifylline Extended-Release Tablets are indicated for the treatment of patients with intermittent claudication on the basis of chronic occlusive arterial disease of the limbs. Pentoxifylline Extended-Release Tablets can improve function and symptoms but is not intended to replace more definitive therapy, such as surgical bypass, or removal of arterial obstructions when treating peripheral vascular disease.

CONTRAINDICATIONS

Pentoxifylline Extended-Release Tablets should not be used in patients with recent cerebral and/or retinal hemorrhage or in patients who have previously exhibited intolerance to this product or methylxanthines such as caffeine, theophylline, and theobromine.

PRECAUTIONS

General

At the first sign of anaphylactic/anaphylactoid reaction, Pentoxifylline Extended-Release Tablets must be discontinued.

Patients with chronic occlusive arterial disease of the limbs frequently show other manifestations of arteriosclerotic disease. Pentoxifylline Extended-Release Tablets have been used safely for treatment of peripheral arterial disease in patients with concurrent coronary artery and cerebrovascular diseases, but there have been occasional reports of angina, hypotension, and arrhythmia. Controlled trials do not show that Pentoxifylline Extended-Release Tablets cause such adverse effects more often than placebo, but, as it is a methylxanthine derivative, it is possible some individuals will experience such responses. Patients on warfarin should have more frequent monitoring of prothrombin times, while patients with other risk factors complicated by hemorrhage (e.g., recent surgery, peptic ulceration, cerebral and/or retinal bleeding) should have periodic examinations for bleeding including, hematocrit and/or hemoglobin.

In patients with hepatic or renal impairment, the exposure to pentoxifylline and/or active metabolites is increased. The consequences of the increase in drug exposure are not known (see Pharmacokinetics and Metabolism and DOSAGE AND ADMINISTRATION).

Drug Interactions

Bleeding has been reported in patients treated with pentoxifylline with or without concomitant NSAIDs, anticoagulants, or platelet aggregation inhibitors.

Increased prothrombin time has been reported in patients concomitantly treated with pentoxifylline and vitamin K antagonists. Monitoring of anticoagulant activity in these patients is recommended when pentoxifylline is introduced or the dose is changed.

Concomitant administration of pentoxifylline and theophylline-containing drugs leads to increased theophylline levels and theophylline toxicity in some individuals. Monitor theophylline levels when starting pentoxifylline or changing dose.

Concomitant administration of strong CYP1A2 inhibitors (including e.g. ciprofloxacin or fluvoxamine) may increase the exposure to pentoxifylline (see ADVERSE REACTIONS).

Pentoxifylline has been used concurrently with antihypertensive drugs, beta blockers, digitalis, diuretics, and antiarrhythmics, without observed problems. Small decreases in blood pressure have been observed in some patients treated with pentoxifylline; periodic systemic blood pressure monitoring is recommended for patients receiving concomitant antihypertensive therapy. If indicated, dosage of the antihypertensive agents should be reduced.

Postmarketing cases of increased anticoagulant activity have been reported in patients concomitantly treated with pentoxifylline and vitamin K antagonists. Monitoring of anticoagulant activity in these patients is recommended when pentoxifylline is introduced or the dose is changed.

Concomitant administration with cimetidine is reported to increase the average steady state plasma concentration of pentoxifylline (~25%) and the Metabolite I (~30%).

Carcinogenesis, Mutagenesis, Impairment of Fertility

Long-term studies of the carcinogenic potential of pentoxifylline were conducted in mice and rats by dietary administration of the drug at doses up to 450 mg/kg (approximately 19 times the maximum recommended human daily dose (MRHD) in both species when based on body weight; 1.5 times the MRHD in the mouse and 3.3 times the MRHD in the rat when based on body surface area). In mice, the drug was administered for 18 months, whereas in rats, the drug was administered for 18 months followed by an additional 6 months without drug exposure. In the rat study, there was a statistically significant increase in benign mammary fibroadenomas in females of the 450 mg/kg group. The relevance of this finding to human use is uncertain. Pentoxifylline was devoid of mutagenic activity in various strains of Salmonella (Ames test) and in cultured mammalian cells (unscheduled DNA synthesis test) when tested in the presence and absence of metabolic activation. It was also negative in the in vivo mouse micronucleus test.

Pregnancy

Teratogenicity studies have been performed in rats and rabbits using oral doses up to 576 and 264 mg/kg, respectively. On a weight basis, these doses are 24 and 11 times the maximum recommended human daily dose (MRHD); on a body-surface-area basis, they are 4.2 and 3.5 times the MRHD. No evidence of fetal malformation was observed. Increased resorption was seen in rats of the 576 mg/kg group. There are no adequate and well controlled studies in pregnant women. Pentoxifylline should be used during pregnancy only if the potential benefit justifies the potential risk to the fetus.

Nursing Mothers

Pentoxifylline and its metabolites are excreted in human milk. Because of the potential for tumorigenicity shown for pentoxifylline in rats, a decision should be made whether to discontinue nursing or discontinue the drug, taking into account the importance of the drug to the mother.

Pediatric Use

Safety and effectiveness in pediatric patients have not been established.

Geriatric Use

Clinical studies of pentoxifylline did not include sufficient numbers of subjects aged 65 and over to determine whether they respond differently from younger subjects. Other reported clinical experience has not identified differences in responses between the elderly and younger patients. In general, dose selection for an elderly patient should be cautious, usually starting at the low end of the dosing range, reflecting the greater frequency of decreased hepatic, renal, or cardiac function, and of concomitant disease or other drug therapy.

The active Metabolite V is known to be substantially excreted by the kidney, and the risk of toxic reactions to this drug may be greater in patients with impaired renal function. Because elderly patients are more likely to have decreased renal function, care should be taken in dose selection, and it may be useful to monitor renal function.

ADVERSE REACTIONS

Clinical trials were conducted using either extended-release pentoxifylline tablets for up to 60 weeks or immediate-release pentoxifylline capsules for up to 24 weeks. Dosage ranges in the tablet studies were 400 mg bid to tid and in the capsule studies, 200 to 400 mg tid. The table summarizes the incidence (in percent) of adverse reactions considered drug related, as well as the numbers of patients who received extended-release pentoxifylline tablets, immediate-release pentoxifylline capsules, or the corresponding placebos. The incidence of adverse reactions was higher in the capsule studies (where dose related increases were seen in digestive and nervous system side effects) than in the tablet studies. Studies with the capsule include domestic experience, whereas studies with the extended-release tablets were conducted outside the U.S.

The table indicates that in the tablet studies few patients discontinued because of adverse effects.

INCIDENCE (%) OF SIDE EFFECTS
 | Extended-Release Tablets |  | Immediate-Release Capsules
 | Commercially Available |  | Used only for Controlled Clinical Trials
 | Pentoxifylline | Placebo | Pentoxifylline | Placebo
(Numbers of Patients at Risk) | (321) | (128) | (177) | (138)
Discontinued for Side Effect | 3.1 | 0 | 9.6 | 7.2
CARDIOVASCULAR SYSTEM
Angina/Chest Pain | 0.3 | - | 1.1 | 2.2
Arrhythmia/Palpitation | - | - | 1.7 | 0.7
Flushing | - | - | 2.3 | 0.7
DIGESTIVE SYSTEM
Abdominal Discomfort | - | - | 4.0 | 1.4
Belching/Flatus/Bloating | 0.6 | - | 9.0 | 3.6
Diarrhea | - | - | 3.4 | 2.9
Dyspepsia | 2.8 | 4.7 | 9.6 | 2.9
Nausea | 2.2 | 0.8 | 28.8 | 8.7
Vomiting | 1.2 | - | 4.5 | 0.7
NERVOUS SYSTEM
Agitation/Nervousness | - | - | 1.7 | 0.7
Dizziness | 1.9 | 3.1 | 11.9 | 4.3
Drowsiness | - | - | 1.1 | 5.8
Headache | 1.2 | 1.6 | 6.2 | 5.8
Insomnia | - | - | 2.3 | 2.2
Tremor | 0.3 | 0.8 | - | ‑
Blurred Vision | - | - | 2.3 | 1.4

Pentoxifylline has been marketed in Europe and elsewhere since 1972. In addition to the above symptoms, the following have been reported spontaneously since marketing or occurred in other clinical trials with an incidence of less than 1%; the causal relationship was uncertain:

Cardiovascular - dyspnea, edema, hypotension.
  Digestive - anorexia, cholecystitis, constipation, dry mouth/thirst.
  Nervous - anxiety, confusion, depression, seizures, aseptic meningitis.
  Respiratory - epistaxis, flu-like symptoms, laryngitis, nasal congestion.
  Skin and Appendages - brittle fingernails, pruritus, rash, urticaria, angioedema.
  Special Senses - blurred vision, conjunctivitis, earache, scotoma.
  Miscellaneous - bad taste, excessive salivation, leukopenia, malaise, sore throat/swollen neck glands, weight change.

A few rare events have been reported spontaneously worldwide since marketing in 1972. Although they occurred under circumstances in which a causal relationship with pentoxifylline could not be established, they are listed to serve as information for physicians. Cardiovascular — angina, arrhythmia, tachycardia. Digestive — hepatitis, jaundice, cholestasis, increased liver enzymes; and Hemic and Lymphatic — decreased serum fibrinogen, pancytopenia, aplastic anemia, leukemia, purpura, thrombocytopenia. Immune system disorders — anaphylactic reaction, anaphylactoid reaction, anaphylactic shock.

To report SUSPECTED ADVERSE REACTIONS, contact ANI Pharmaceuticals, Inc. at 1-855-204-1431 or FDA at 1-800-FDA-1088 or www.fda.gov/medwatch.

OVERDOSAGE

Overdosage with pentoxifylline has been reported in pediatric patients and adults. Symptoms appear to be dose related. A report from a poison control center on 44 patients taking overdoses of enteric-coated pentoxifylline extended-release tablets noted that symptoms usually occurred 4‑ 5 hours after ingestion and lasted about 12 hours. The highest amount ingested was 80 mg/kg; flushing, hypotension, convulsions, somnolence, loss of consciousness, fever, and agitation occurred. All patients recovered. In addition to symptomatic treatment and gastric lavage, special attention must be given to supporting respiration, maintaining systemic blood pressure, and controlling convulsions. Activated charcoal has been used to absorb pentoxifylline in patients who have overdosed.

DOSAGE AND ADMINISTRATION

The usual dosage of pentoxifylline in extended-release tablet form is one tablet (400 mg) three times a day with meals.

While the effect of pentoxifylline may be seen within 2 to 4 weeks, it is recommended that treatment be continued for at least 8 weeks. Efficacy has been demonstrated in double-blind clinical studies of 6 months duration.

Digestive and central nervous system side effects are dose related. If patients develop these effects it is recommended that the dosage be lowered to one tablet twice a day (800 mg/day). If side effects persist at this lower dosage, the administration of pentoxifylline should be discontinued.

In patients with severe renal impairment (creatinine clearance below 30 mL/min) reduce dose to 400 mg once a day.

Dosing information cannot be provided for patients with hepatic impairment.

HOW SUPPLIED

Pentoxifylline Extended-Release Tablets USP, 400 mg are available for oral administration as yellow, oblong, film-coated tablets, embossed with “N668” on one side and plain on the other. They are supplied in bottles of 100 (NDC 70954-668-10) and bottles of 500 (NDC 70954-668-20).

Store at 20° to 25°C (68° to 77°F) [see USP Controlled Room Temperature].

Dispense in a tight, light-resistant container as defined in the USP.

Rx only

Distributed by:
ANI Pharmaceuticals, Inc.
Baudette, MN 56623

Issued: 05/2025
LB4581-01

PACKAGE/LABEL PRINCIPAL DISPLAY PANEL

NDC 70954-668-10
Pentoxifylline Extended-Release Tablets USP
400 mg
Rx only
100 Tablets